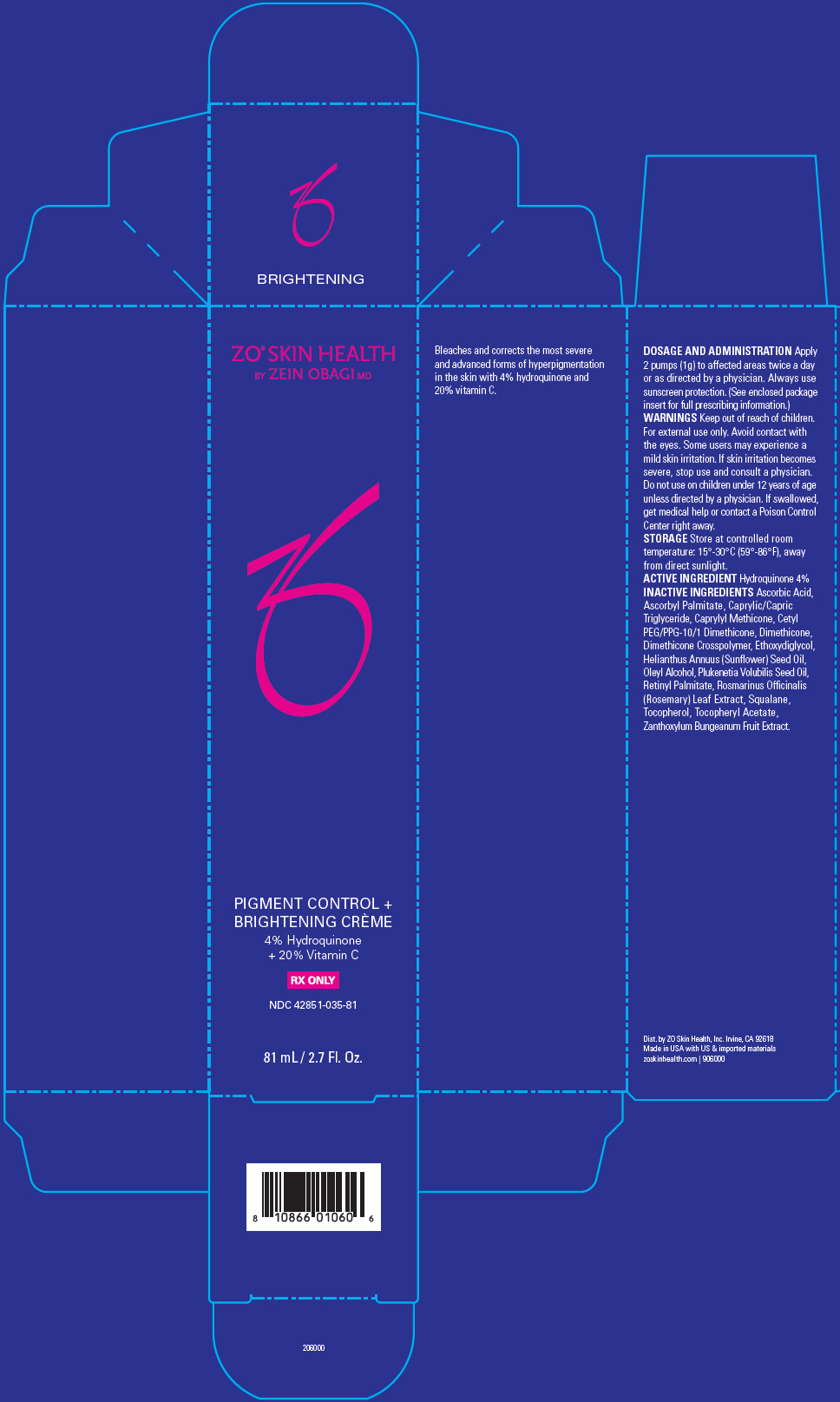 DRUG LABEL: ZO Skin Health Pigment Control plus Brightening Creme Hydroquinone plus Vitamin C
NDC: 42851-035 | Form: EMULSION
Manufacturer: ZO Skin Health, Inc.
Category: prescription | Type: HUMAN PRESCRIPTION DRUG LABEL
Date: 20220421

ACTIVE INGREDIENTS: HYDROQUINONE 0.04 mg/1 mL
INACTIVE INGREDIENTS: ASCORBIC ACID; ASCORBYL PALMITATE; MEDIUM-CHAIN TRIGLYCERIDES; CAPRYLYL TRISILOXANE; CETYL PEG/PPG-10/1 DIMETHICONE (HLB 2); DIMETHICONE; DIMETHICONE CROSSPOLYMER (450000 MPA.S AT 12% IN CYCLOPENTASILOXANE); DIETHYLENE GLYCOL MONOETHYL ETHER; SUNFLOWER OIL; OLEYL ALCOHOL; PLUKENETIA VOLUBILIS SEED OIL; VITAMIN A PALMITATE; ROSEMARY; SQUALANE; TOCOPHEROL; .ALPHA.-TOCOPHEROL ACETATE; ZANTHOXYLUM BUNGEANUM FRUIT

ZO® Skin Health Pigment Control + Brightening Crème 4% Hydroquinone + 20% Vitamin C
National Drug Code 42851-035-##

DOSAGE AND ADMINISTRATION

Apply 2 pumps (1g) to affected areas twice a day or as directed by a physician. Always use sunscreen protection. (See enclosed package insert for full prescribing information.)

WARNINGS

Keep out of reach of children. For external use only. Avoid contact with the eyes. Some users may experience a mild skin irritation. If skin irritation becomes severe, stop use and consult a physician. Do not use on children under 12 years of age unless directed by a physician. If swallowed, get medical help or contact a Poison Control Center right away.

STORAGE

Store at controlled room temperature: 15°-30°C (59°-86°F), away from direct sunlight.

ACTIVE INGREDIENT

Hydroquinone 4%

INACTIVE INGREDIENTS

Ascorbic Acid, Ascorbyl Palmitate, Caprylic/Capric Triglyceride, Caprylyl Methicone, Cetyl PEG/PPG-10/1 Dimethicone, Dimethicone, Dimethicone Crosspolymer, Ethoxydiglycol, Helianthus Annuus (Sunflower) Seed Oil, Oleyl Alcohol, Plukenetia Volubilis Seed Oil, Retinyl Palmitate, Rosmarinus Officinalis (Rosemary) Leaf Extract, Squalane, Tocopherol, Tocopheryl Acetate, Zanthoxylum Bungeanum Fruit Extract.

Bleaches and corrects the most severe and advanced forms of hyperpigmentation in the skin with 4% hydroquinone and 20% vitamin C.

Dist. by ZO Skin Health, Inc. Irvine, CA 92618
Made in USA with US & imported materials zoskinhealth.com | 906000

PRINCIPAL DISPLAY PANEL - 81 mL Bottle Carton

ZO® SKIN HEALTH
BY ZEIN OBAGI MD

PIGMENT CONTROL +
BRIGHTENING CRÈME

4% Hydroquinone
+ 20% Vitamin C

RX ONLY

NDC 42851-035-81

81 mL / 2.7 Fl. Oz.